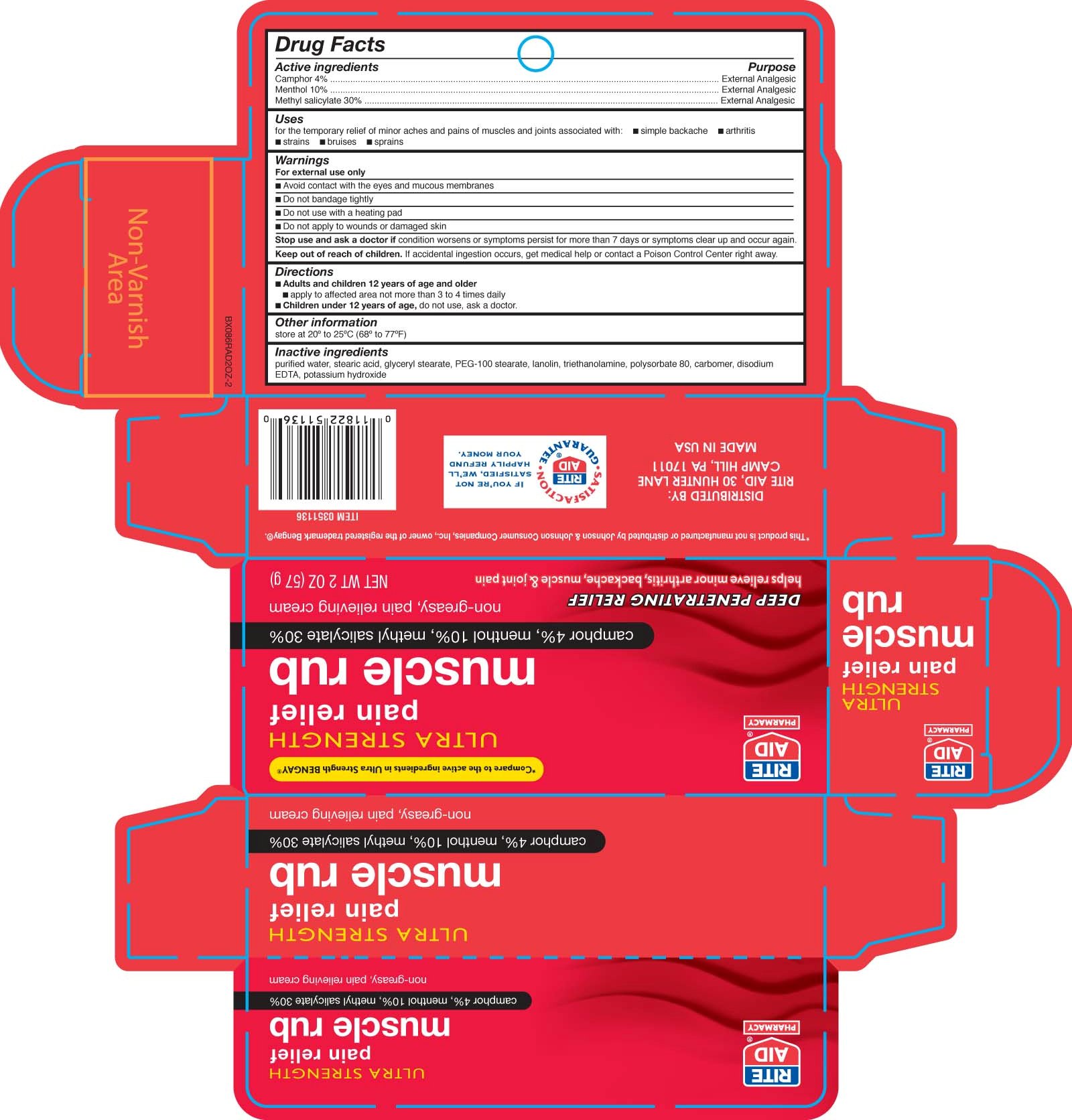 DRUG LABEL: Rite Aid Ultra Strength Muscle Rub
NDC: 11822-0406 | Form: OINTMENT
Manufacturer: RITE AID CORPORATION
Category: otc | Type: HUMAN OTC DRUG LABEL
Date: 20110328

ACTIVE INGREDIENTS: MENTHOL 100 mg/1 g; CAMPHOR (SYNTHETIC) 40 mg/1 g; METHYL SALICYLATE 300 mg/1 g
INACTIVE INGREDIENTS: WATER; CARBOMER HOMOPOLYMER TYPE C; GLYCERYL MONOSTEARATE; EDETATE DISODIUM; TROLAMINE; LANOLIN; POTASSIUM HYDROXIDE; POLYSORBATE 80; STEARIC ACID

DRUG FACTS

Active ingredient Purpose
Camphor 4%......................................................External Analgesic
Menthol 10%......................................................External Analgesic
Methyl Salicylate 30%.........................................External Analgesic

Uses
For the temporary relief of minor aches and pains of muscles and joints associated with:
- simple backache - arthritis - strains - bruises - sprains

Keep out of reach of children. If swallowed, get medical help or contact a
Poison Control Center right away.

Uses
For the temporary relief of minor aches and pains of muscles and joints associated with:
- simple backache - arthritis - strains - bruises - sprains

Warnings
For external use only
- avoid contact with eyes and mucous membranes
- do not bandage tightly
- do not use with a heating pad
- do not apply to wounds or damaged skin
Stop use and ask a doctor if condition worsens or symptoms persist for more than 7 days or symptoms clear up and occur again.
Keep out of reach of children.If swallowed, get medical help or contact a Poison Control Center right away.

Directions
- Adults and children 12 years of age and older
- apply to affected area not more than 3 to 4 times daily
- Children under 12 years of age do not use, ask a doctor.
Other information store at 20 degrees to 25 degrees C (68 degrees to 77 degrees F)

Inactive Ingredients
purified water, stearic acid, glyceryl stearate, PEG-100 stearate, lanolin, triethanolamine, polysorbate 80, carbomer, disodium EDTA, potassium hydroxide